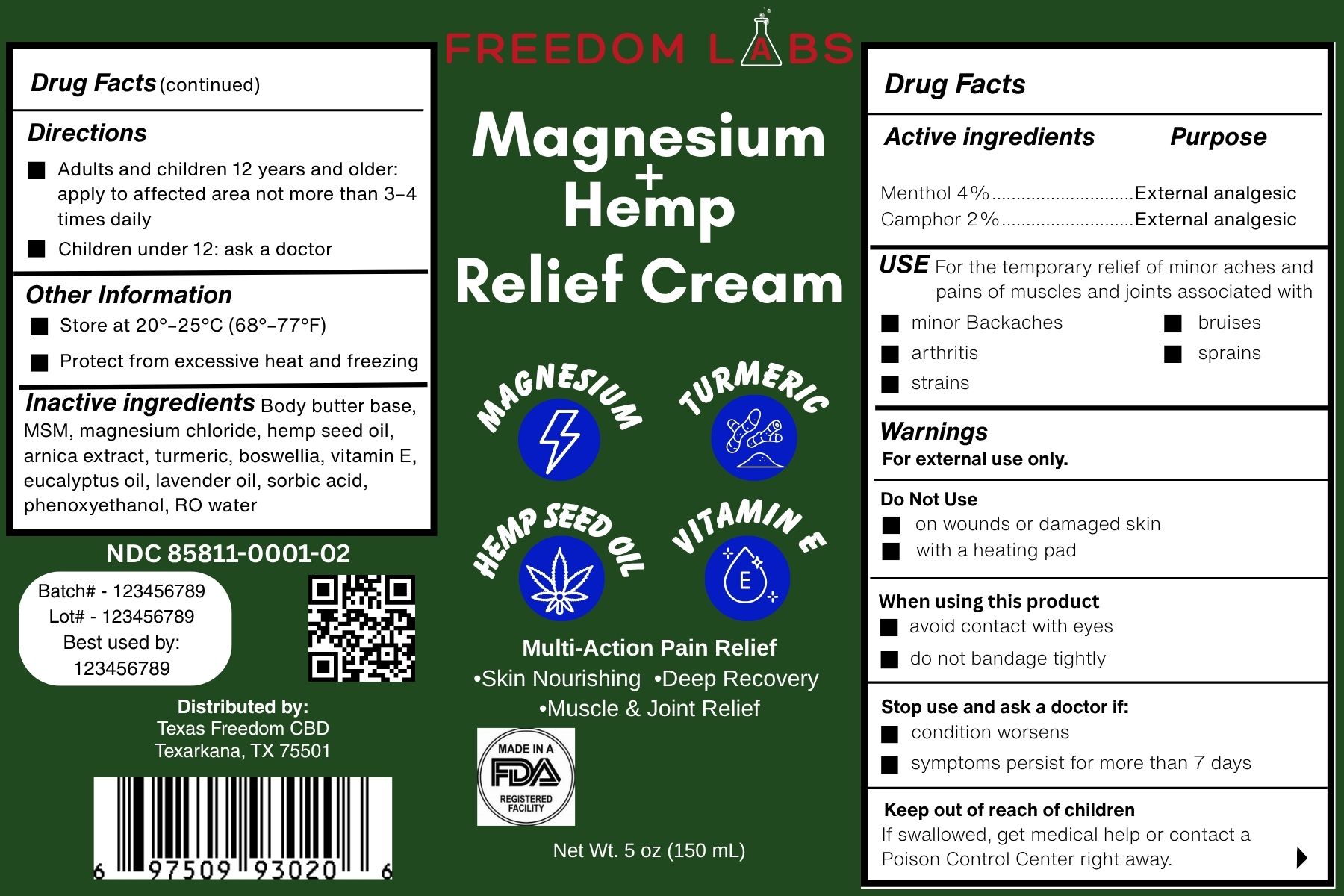 DRUG LABEL: Freedom Labs
NDC: 85811-0001 | Form: CREAM
Manufacturer: TEXAS FREEDOM CBD, LLC
Category: otc | Type: HUMAN OTC DRUG LABEL
Date: 20250612

ACTIVE INGREDIENTS: CAMPHOR (NATURAL) 20 mg/1000 mg; MENTHOL 40 mg/1000 mg
INACTIVE INGREDIENTS: CURCUMA LONGA (TURMERIC) ROOT POWDER; DIMETHYL SULFONE; CANNABIS SATIVA SEED OIL; ARNICA MONTANA FLOWER; EUCALYPTUS GLOBULUS LEAF OIL; MAGNESIUM CHLORIDE; LAVANDULA ANGUSTIFOLIA (LAVENDER) OIL; PHENOXYETHANOL; BOSWELLIA SERRATA GUM; ALPHA-TOCOPHEROL ACETATE; SORBIC ACID; WATER

Directions

Adults and children 12 years and older: apply to affected area not more than 3–4 times daily

Children under 12: ask a doctor

Warnings

For external use only.

Do Not Use

on wounds or damaged skin

When using this product

avoid contact with eyes

do not bandage tightly

Stop use and ask a doctor if:

condition worsens

symptoms persist for more than 7 days

Keep out of reach of children

If swallowed, get medical help or contact a Poison Control Center right away.

Inactive ingredient

Body butter base,

MSM,

magnesium chloride,

hemp seed oil,

arnica extract,

turmeric,

boswellia,

vitamin E,

eucalyptus oil,

lavender oil,

sorbic acid,

phenoxyethanol,

RO water

Keep out of reach of children

If swallowed, get medical help or

contact a Poison Control Center right away.

Active ingredients

Menthol 4%.............................External analgesic

Camphor 2%...........................External analgesic

Indications & Usage

“For the temporary relief of minor aches and pains of muscles and joints associated with backaches, arthritis, strains, sprains, and bruises.”